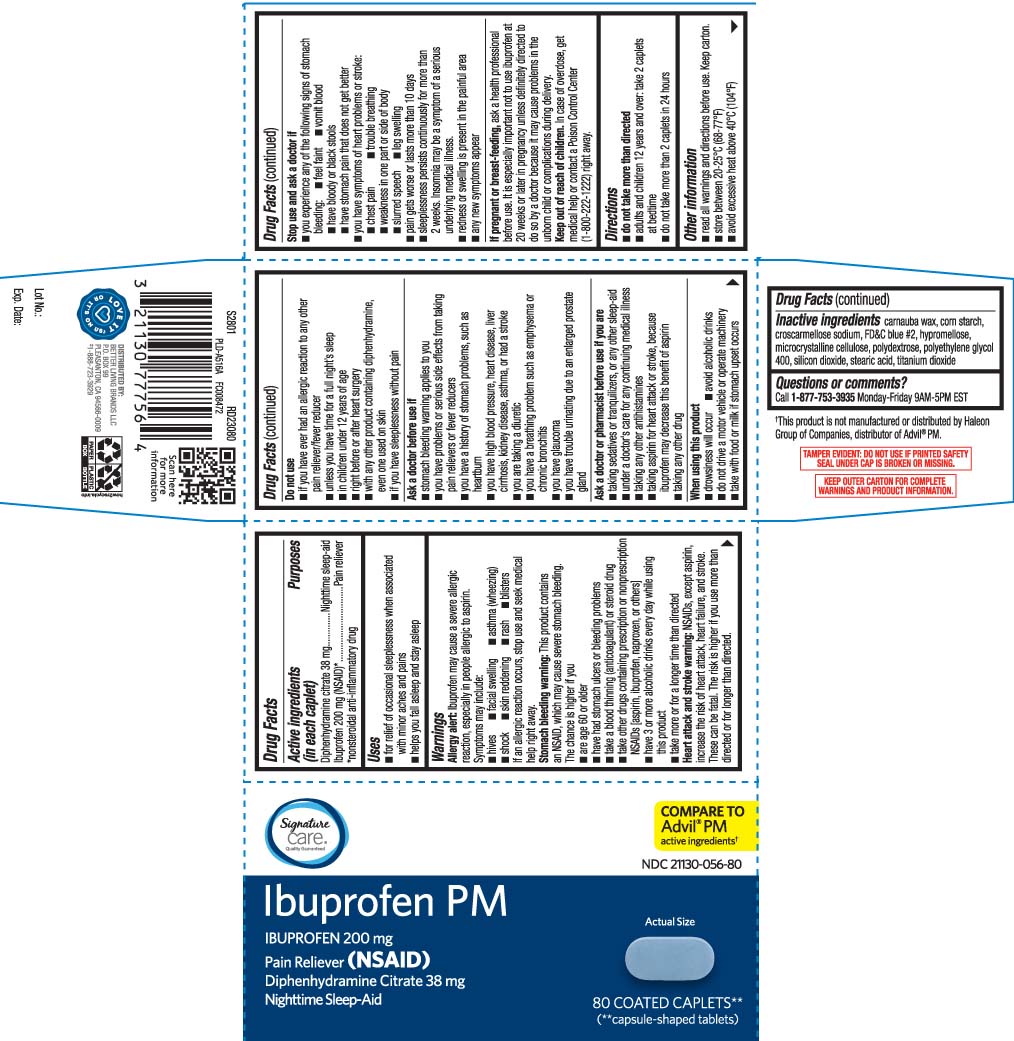 DRUG LABEL: Ibuprofen PM
NDC: 21130-056 | Form: TABLET, COATED
Manufacturer: Safeway, Inc.
Category: otc | Type: HUMAN OTC DRUG LABEL
Date: 20260105

ACTIVE INGREDIENTS: IBUPROFEN 200 mg/1 1; DIPHENHYDRAMINE CITRATE 38 mg/1 1
INACTIVE INGREDIENTS: CARNAUBA WAX; STARCH, CORN; CROSCARMELLOSE SODIUM; FD&C BLUE NO. 2; HYPROMELLOSE, UNSPECIFIED; CELLULOSE, MICROCRYSTALLINE; POLYDEXTROSE; POLYETHYLENE GLYCOL 400; SILICON DIOXIDE; STEARIC ACID; TITANIUM DIOXIDE

Drug Facts

Active ingredient (in each caplet)

Diphenhydramine citrate 38 mg

ibuprofen 200 mg(NSAID)*

*nonsteroidal anti-inflammatory drug

Purpose

Nighttime sleep-aid

Pain Reliever

Uses

- for relief of occasional sleeplessness when associated with minor aches and pains
- helps you fall asleep and stay asleep

Warnings

Allergy alert: Ibuprofen may cause a severe allergic reaction, especially in people allergic to aspirin. Symptoms may include:

- hives
- facial swelling
- asthma (wheezing)
- shock
- skin reddening
- rash
- blisters

If an allergic reaction occurs, stop use and seek medical help right away.

Stomach bleeding warning: This product contains an NSAID, which may cause severe stomach bleeding. The chance is higher if you:

- are age 60 or older
- have had stomach ulcers or bleeding problems
- take a blood thinning (anticoagulant) or steroid drug
- take other drugs containing prescription or nonprescription NSAIDs [aspirin, ibuprofen, naproxen, or others]
- have 3 or more alcoholic drinks every day while using this product
- take more or for a longer time than directed

Heart attack and stroke warning: NSAIDs, except aspirin, increase the risk of heart attack, heart failure, and stroke. These can be fatal. The risk is higher if you use more than directed or for longer than directed

Do not use

- if you have ever had an allergic reaction to any other pain reliever/fever reducer
- unless you have time for a full night’s sleep
- in children under 12 years of age
- right before or after surgery
- with any other product containing diphenhydramine, even one used on skin
- if you have sleeplessness without pain

Ask a doctor before use if

- the stomach bleeding warning applies to you
- you have problem or serious side effects from taking pain relievers or fever reducers
- you have a history of stomach problems, such as heartburn
- you have high blood pressure, heart disease, liver cirrhosis, kidney disease, or asthma or had a stroke
- you are taking a diuretic
- you have a breathing problem such as emphysema or chronic bronchitis
- you have glaucoma
- you have trouble urinating due to an enlarged prostate gland

Ask a doctor or pharmacist before use if you are

- taking sedatives or tranquilizers, or any other sleep-aid
- under a doctor's care for any continuing medical illness
- taking any other antihistamines
- taking aspirin for heart attack or stroke, because ibuprofen may decease this benefit of aspirin
- taking any other drug

When using this product

- drowsiness will occur
- avoid alcoholic drinks
- do not drive a motor vehicle or operate machinery
- take with food or milk if stomach upset occurs

Stop use and ask a doctor if

- you experience any of the following signs of stomach bleeding:
  - feel faint
  - vomit blood
  - have bloody or black stools
  - have stomach pain that does not get better
- you have symptoms of heart problem or stroke:
  - chest pain
  - trouble breathing
  - weakness in one part or side of body
  - slurred speech
  - leg swelling
- pain gets worse or last more than 10 days
- sleeplessness persists continuously for more than 2 weeks. Insomnia may be a symptom of a serious underlying medical illness
- redness or swelling is present in the painful area
- any new symptoms appear

If pregnant or breast-feeding,

ask a health professional before use. It is especially important not to use ibuprofen at 20 weeks or later in pregnancy unless definitely directed to do so by a doctor because it may cause problems in the unborn child or complications during delivery.

Keep out of reach of children.

In case of overdose, get medical help or contact a Poison Control Center (1-800-222-1222) right away.

Directions

- do not take more than directed
- adults and childlren 12 years and over: take 2 caplets at bedtime
- do not take more than 2 caplets in 24 hours

Other information

- read all warnings and directions before use. Keep carton.
- store between 20-25°C (68-77°F)
- avoid excessive heat above 40°C (104°F)

Inactive ingredients

carnauba wax, corn starch, croscarmellose sodium,FD&C blue #2, hypromellose, microcrystalline cellulose, polydextrose, polyethylene glycol 400, silicon dioxide, stearic acid, titanium dioxide

Questions or comments?

Call 1-877-753-3935 Monday-Friday 9AM-5PM EST

Principal Display Panel

COMPARE TO Advil® PM active ingredients†

Ibuprofen PM

IBUPROFEN 200 mg

Pain reliever (NSAID)

Diphenhydramine citrate 38 mg

Nighttime sleep-aid

COATED CAPLETS**

(**capsules-shaped tablets)

†This product is not manufactured or distributed by Haleon Group of Companies, distributor Advil® PM

TAMPER EVIDENT: DO NOT USE IF PRINTED SAFETY SEAL UNDER CAP IS BROKEN OR MISSING.

KEEP OUTER CARTON FOR COMPLETE WARNINGS AND PRODUCT INFORMATION.

DISTRIBUTED BY

BETTER LIVING BRANDS LLC

P.O. BOX 99

PLEASANTON, CA 94566-0009

Product Packaging

SIGNATURE CARE Ibuprofen PM